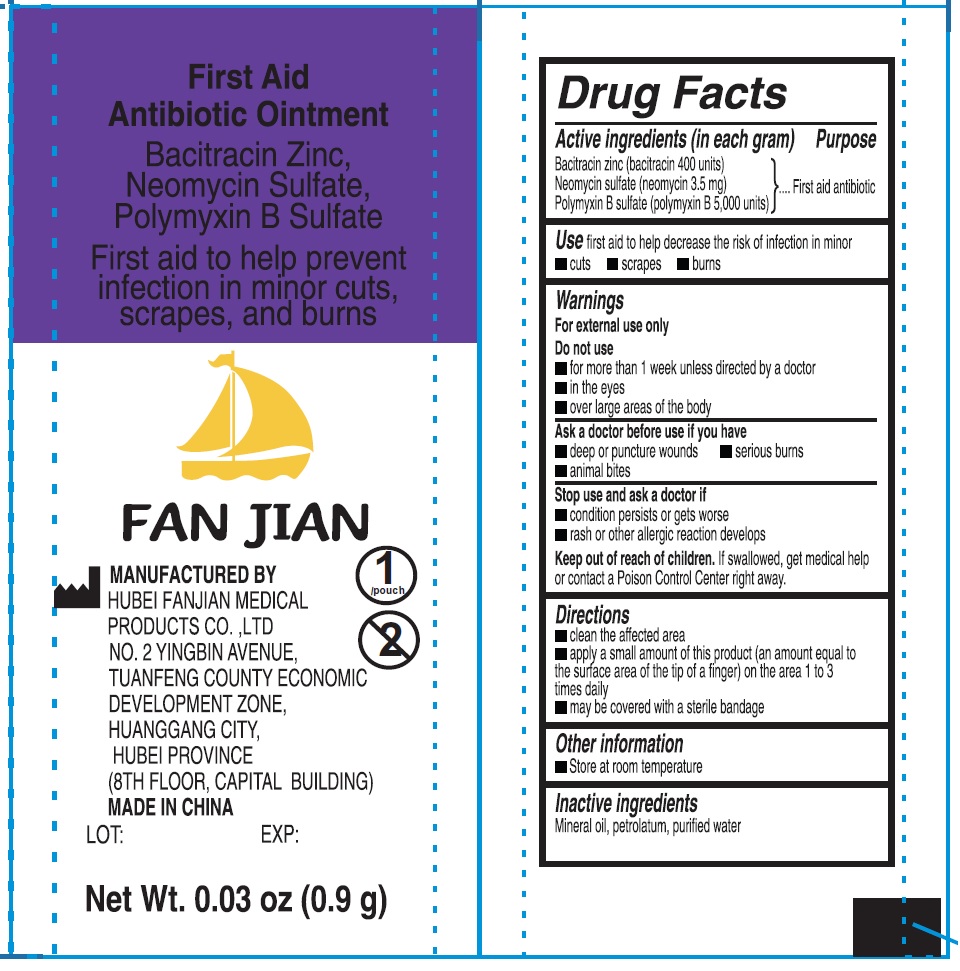 DRUG LABEL: First Aid Antibiotic
NDC: 83165-005 | Form: LIQUID
Manufacturer: Hubei Fanjian Medical Product Co.,Ltd
Category: otc | Type: HUMAN OTC DRUG LABEL
Date: 20231110

ACTIVE INGREDIENTS: BACITRACIN ZINC 400 U/1 g; NEOMYCIN SULFATE 3.5 mg/1 g; POLYMYXIN B SULFATE 5000 U/1 g
INACTIVE INGREDIENTS: MINERAL OIL; PETROLATUM; WATER

First Aid Antibiotic Ointment

Active ingredients (in each gram)

Bacitracin zinc (bacitracin 400 units)

Neomycin sulfate (neomycin 3.5 mg)

Polymyxin B sulfate (polymyxin B 5,000 units)

Purpose

First aid antibiotic

Uses

first aid to help decrease the risk of infection in minor

• cuts • scrapes • burns

Warnings

For external use only

Do not use

• for more than 1 week unless directed by a doctor

• in the eyes

• over large areas of the body

Ask a doctor before use if you have

• deep or puncture wounds • serious burns • animal bites

Stop use and ask a doctor if

• condition persists or gets worse

• rash or other allergic reaction develops

Keep out of reach of children.

If swallowed, get medical help or contact a Poison Control Center right away.

Directions

• clean the affected area

• apply a small amount of this product (an amount equal to the surface area of the tip of a finger) on the area 1 to 3 times daily

• may be covered with a sterile bandage

Other information

• Store at room temperature

Inactive ingredients

Mineral oil, petrolatum, purified water